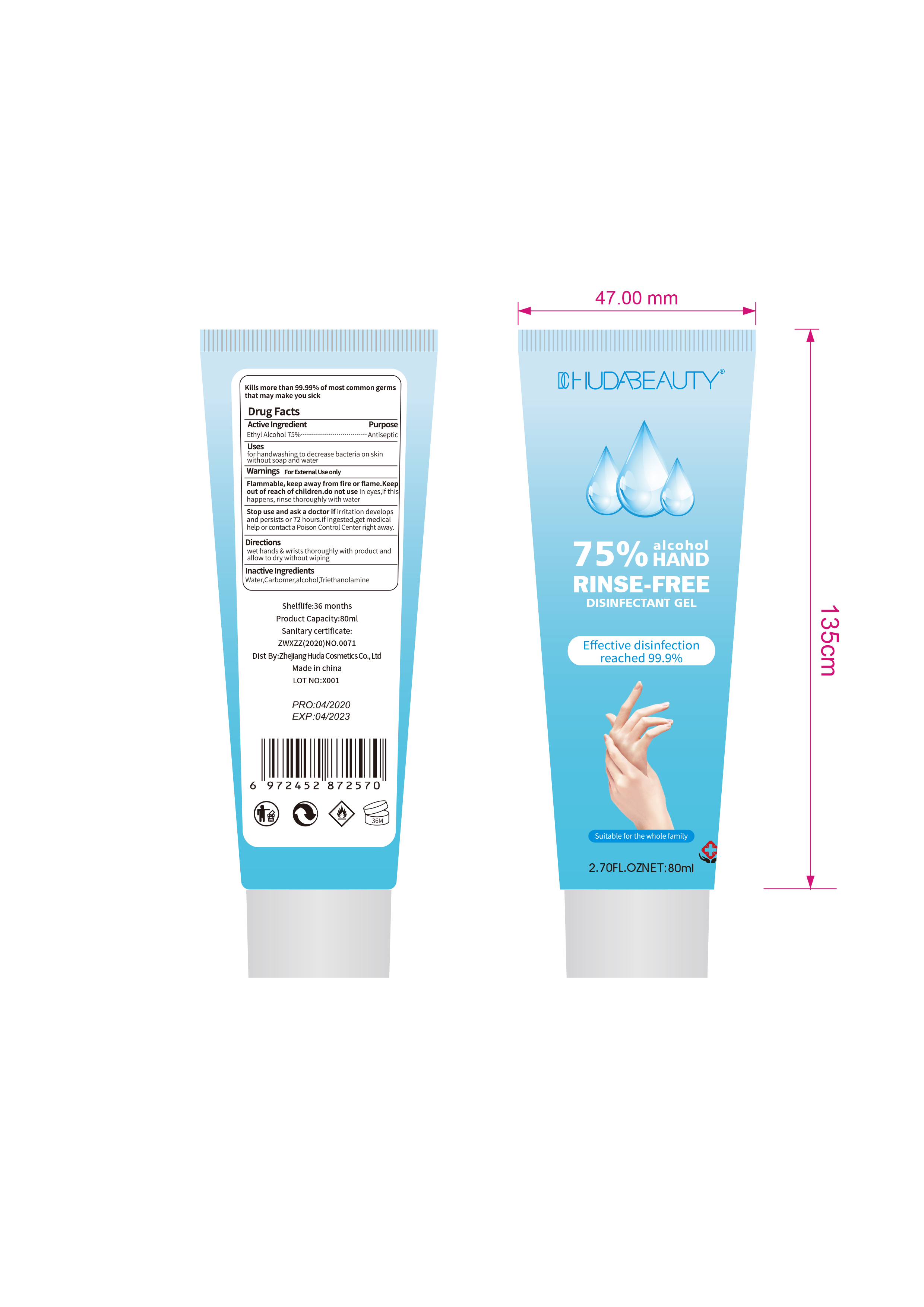 DRUG LABEL: DC HUDABeauty 75% Alcohol Hand Rinse Free Disinfectant
NDC: 75511-002 | Form: GEL
Manufacturer: ZHEJIANG HUDA COSMETICS CO., LTD.
Category: otc | Type: HUMAN OTC DRUG LABEL
Date: 20200426

ACTIVE INGREDIENTS: ALCOHOL 75 mL/100 mL
INACTIVE INGREDIENTS: CARBOMER 934; TRIETHANOLAMINE SULFATE

NA

Active Ingredient(s)

Alcohol 75% v/v. Purpose: Antiseptic

Purpose

Antiseptic

Use

For hand washing to decrease bacteria on the skin without soap and water

Warnings

For external use only.

Flammable. Keep away from heat and flame

Do not use in eyes, if this happens, rinse thoroughly with water

Stop use and ask a doctor if irritation develops and persists for more than 72 hours. If ingested, get medical help or contact a poison control center right away

Keep out of reach of children.

Directions

- Wet hands thoroughly with product and allow to dry without wiping

Inactive ingredients

Water, Carbomer, Triethanolamine